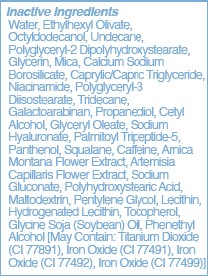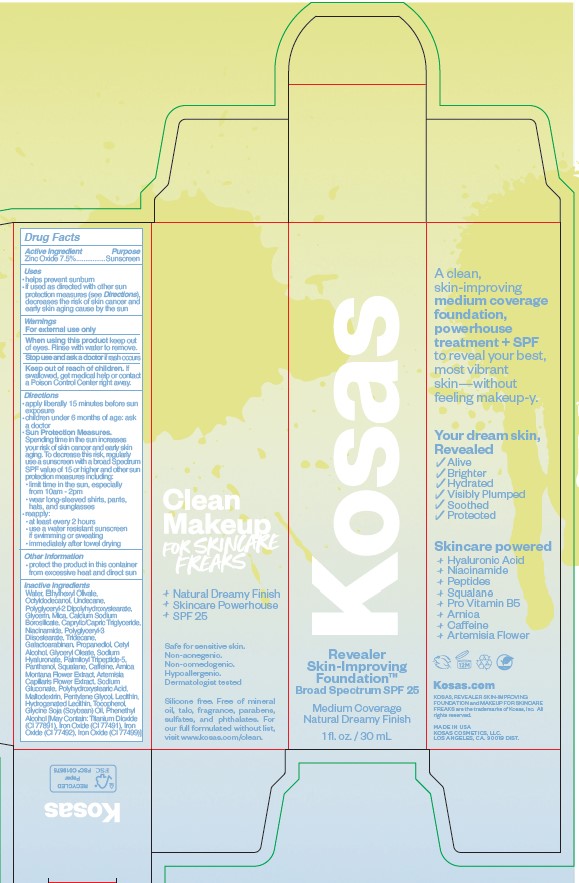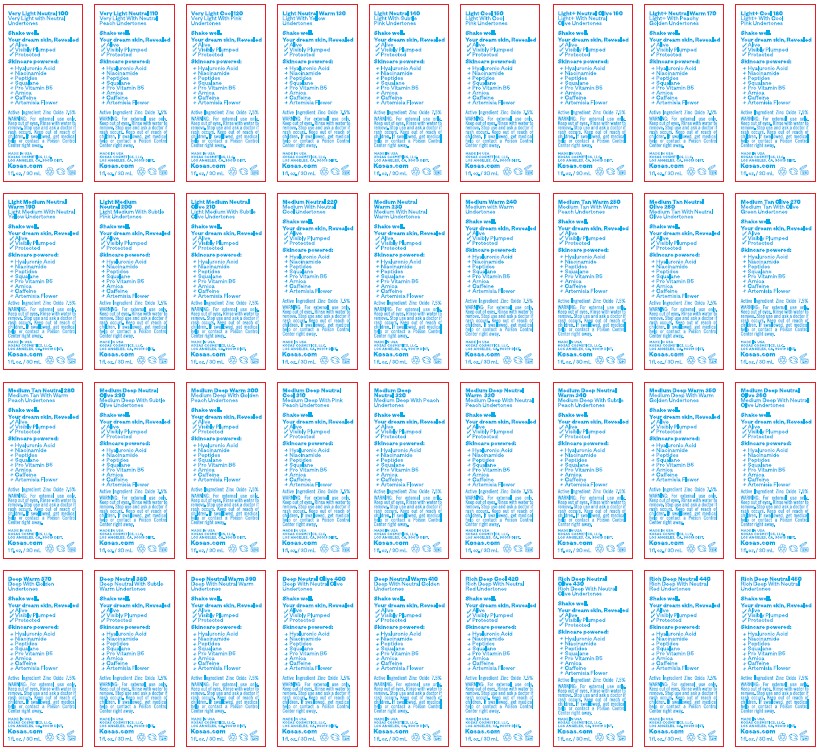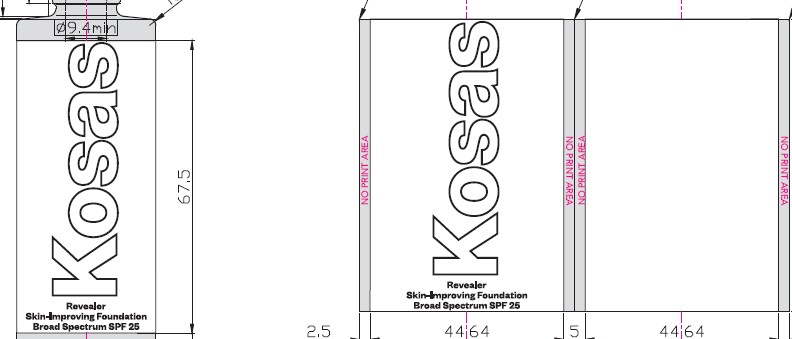 DRUG LABEL: Revealer Skin-Improving Foundation
NDC: 82554-104 | Form: LOTION
Manufacturer: Kosas Cosmetics, LLC
Category: otc | Type: HUMAN OTC DRUG LABEL
Date: 20250213

ACTIVE INGREDIENTS: ZINC OXIDE 7.5 g/100 mL
INACTIVE INGREDIENTS: TRIDECANE; OCTYLDODECANOL; ETHYLHEXYL OLIVATE; PHENETHYL ALCOHOL; CALCIUM SODIUM BOROSILICATE; FERRIC OXIDE RED; SODIUM GLUCONATE; MALTODEXTRIN; PENTYLENE GLYCOL; TITANIUM DIOXIDE; MEDIUM-CHAIN TRIGLYCERIDES; MICA; POLYGLYCERYL-2 DIPOLYHYDROXYSTEARATE; GLYCERIN; PROPANEDIOL; HYALURONATE SODIUM; LECITHIN, SOYBEAN; GALACTOARABINAN; WATER; CETYL ALCOHOL; PANTHENOL; CAFFEINE; ARTEMISIA CAPILLARIS FLOWER; POLYGLYCERYL-3 DIISOSTEARATE; NIACINAMIDE; TOCOPHEROL; ARNICA MONTANA FLOWER; GLYCINE SOJA (SOYBEAN) OIL; UNDECANE; GLYCERYL OLEATE; PALMITOYL TRIPEPTIDE-5; SQUALANE; POLYHYDROXYSTEARIC ACID (2300 MW)

Directions

Apply liberally 15 minutes before sun exposure
Children under 6 months of age: ask a doctor

Sun Protection Measures:

Spending time in the sun
increases your risk of skin cancer and early skin aging.
Decrease this risk, regularly use a sunscreen with a broad
Spectrum SPF value of 15 or higher and other sun protection
measures including: limit time in the sun, especially from 10am - 2pm, wear long-sleeved shirts, pants, hats, and sunglasses, and reapply after 80 minutes of swimming or sweating, immediately after towel drying, at least every 2 hours

Warnings

For external use only
When using this product keep out of eyes. Rinse with water to remove.
Stop use and ask a doctor if rash occurs.
Keep out of reach of children. If swallowed, get medical
help or contact a Poison Control Center right away.

Do not use on damaged or broken skin.

Use

Uses:

Helps prevent sunburn if used as directed with other sun protection measures (see Directions), decreases the risk of skin cancer and early skin aging caused by the sun.

Keep out of reach of children. If swallowed, get medical help or contact a Poison Control Center right away.

Purpose

Sunscreen